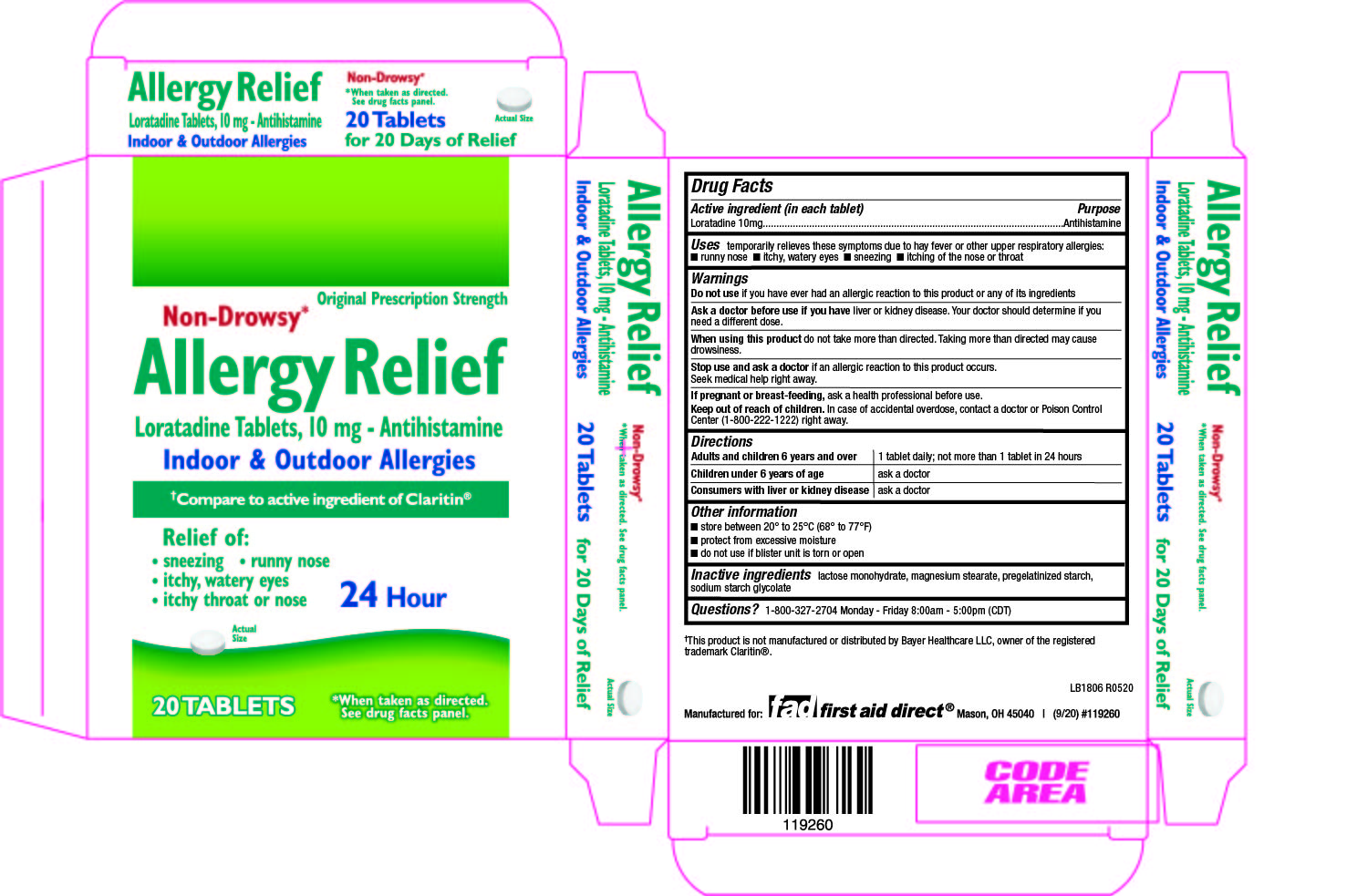 DRUG LABEL: Allergy Relief
NDC: 53117-414 | Form: TABLET
Manufacturer: First Aid Direct
Category: otc | Type: HUMAN OTC DRUG LABEL
Date: 20201112

ACTIVE INGREDIENTS: LORATADINE 10 mg/1 1
INACTIVE INGREDIENTS: LACTOSE MONOHYDRATE; MAGNESIUM STEARATE; STARCH, CORN; SODIUM STARCH GLYCOLATE TYPE A

414-Allergy Relief

Active ingredient(s)

Loratadine 10mg

Purpose

Antihistamine

Use(s)

temporarily relieves these symptoms due to hay fever or other upper respiratory allergies:

- runny nose
- itchy, watery eyes
- sneezing
- itching of the nose or throat

Warnings

Do not use

if you have ever had an allergic reaction to this product or any of its ingredients

Ask a doctor before use if

or kidney disease. Your doctor should determine if you need a different dose.

When using this product

do not take more than directed. Taking more than directed may cause drowsiness.

Stop use and ask a doctor if

if an allergic reaction to this product occurs. Seek medical help right away.

Keep out of reach of children

In case of accidental overdose, contact a doctor or Poison Control Center (1-800-222-1222) right away.

Directions

Adults and children 6 years and over 1 tablet daily; not more than 1 tablet in 24 hours
Children under 6 years of age ask a doctor
Consumers with liver or kidney disease ask a doctor

Other information

- do not use if blister unit is torn or

Storage

- store between 20° to 25°C (68° to 77°F)
- protect from excessive moisture

Inactive ingredients

lactose monohydrate, magnesium stearate, pregelatinized starch, sodium starch glycolate

Questions

1-800-327-2704 Monday - Friday 8:00am - 5:00pm (CDT)

Principal Display Panel

Allergy Relief Loratadine